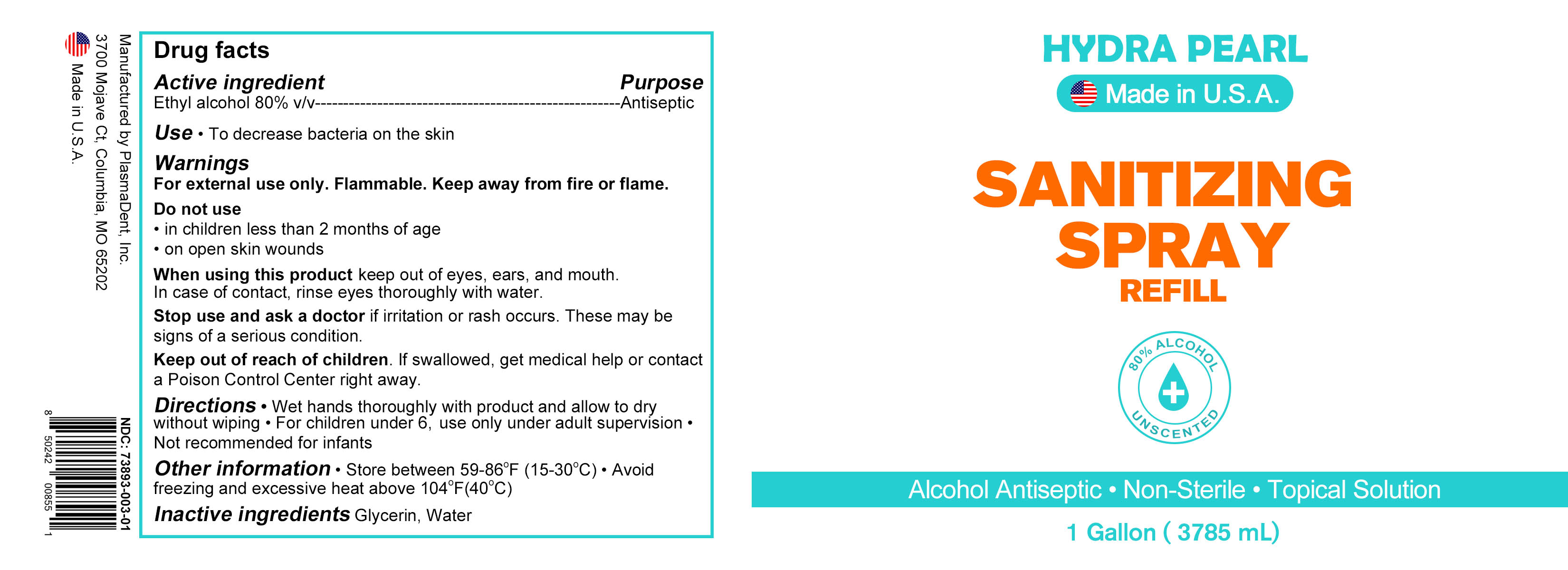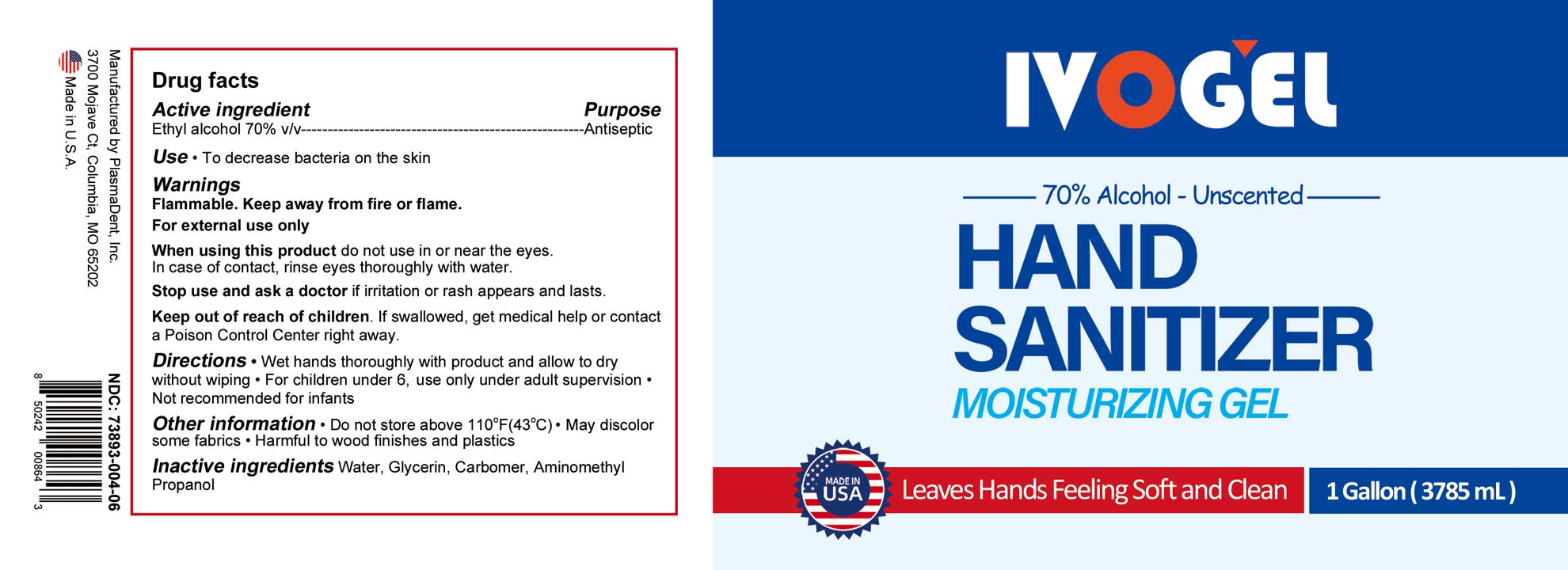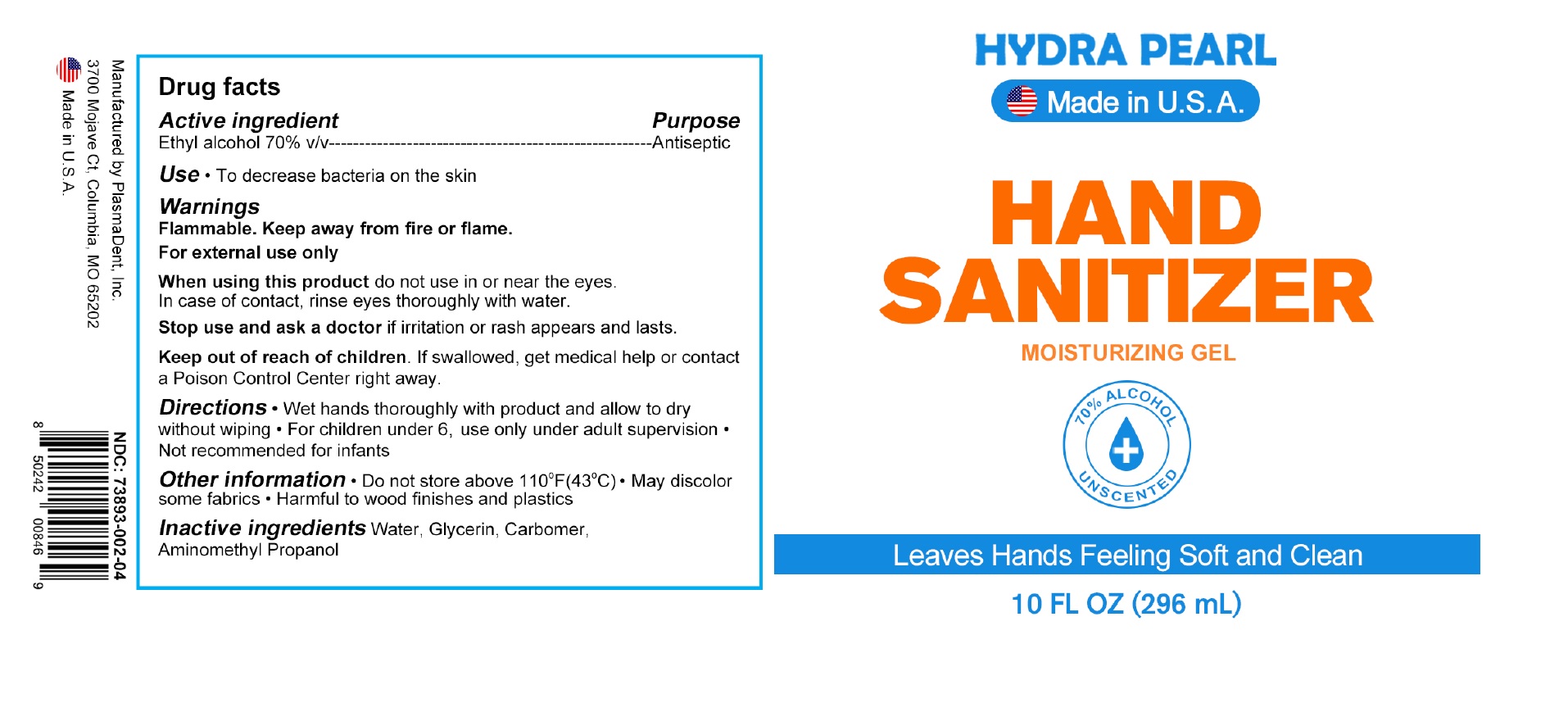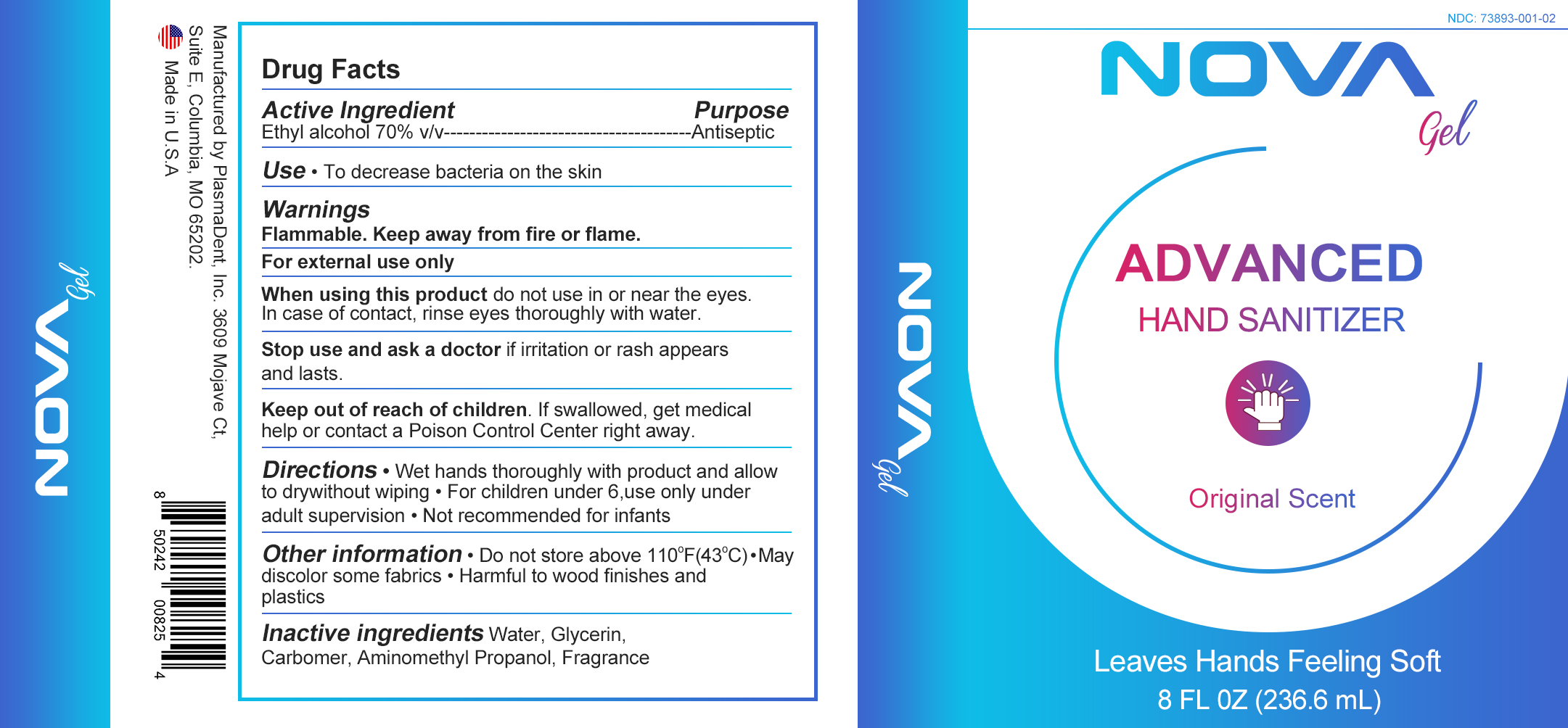 DRUG LABEL: Hydra Pearl Hand Sanitizer
NDC: 73893-002 | Form: GEL
Manufacturer: PlasmaDent Inc
Category: otc | Type: HUMAN OTC DRUG LABEL
Date: 20220225

ACTIVE INGREDIENTS: ALCOHOL 70 mL/100 mL
INACTIVE INGREDIENTS: AMINOMETHYLPROPANOL 0.1 g/100 mL; GLYCERIN 2 g/100 mL; CARBOMER HOMOPOLYMER, UNSPECIFIED TYPE 0.3 g/100 mL; WATER 32.8 g/100 mL

Nova Gel

Advanced Hand Sanitizer

Original Scent

Leaves Hands Feeling Soft

8 FL OZ (236.6 mL)

Active Ingredient

Active Ingredient Purpose

Ethyl Alcohol 70% v/v ----------------Antiseptic

Purpose

Use- To decrease bacteria on the skin

Use

Use-To decrease bacteria on the skin

Keep out of the reach of children

Warnings

Flammable. Keep away from fire or flame.

For external use only

When using this product do not use in or near the eyes. In case of contact, rinse eyes thoroughly with water.

Stope use and ask a doctor if irritation or rash appears and lasts.

Keep out of reach of children. If swallowed get medical help or contact a poisen control center right away.

Directions

Directions-wet hands thoroughly with product and allow to dry without wiping. For children under 6 use only under adult supervision. Not recommended for infants.

Other information

Other information- Do not store above 110oF (43oC)

May discolor some fabrics.

Harmful to wood finishes and plastics

Inactive Ingredient Section

Inactive Ingredient- Water, Glycerin, Carbomer, Aminomethyl propanol, fragrance

Hydra Pearl

Advanced Hand Sanitizer

Original Scent

Leaves Hands Feeling Soft

8 FL OZ (236.6 mL)

Ivogel Hand Sanitizer

70% Alcohol Unscented

Moisterizing Gel

Leaves hands feeling soft